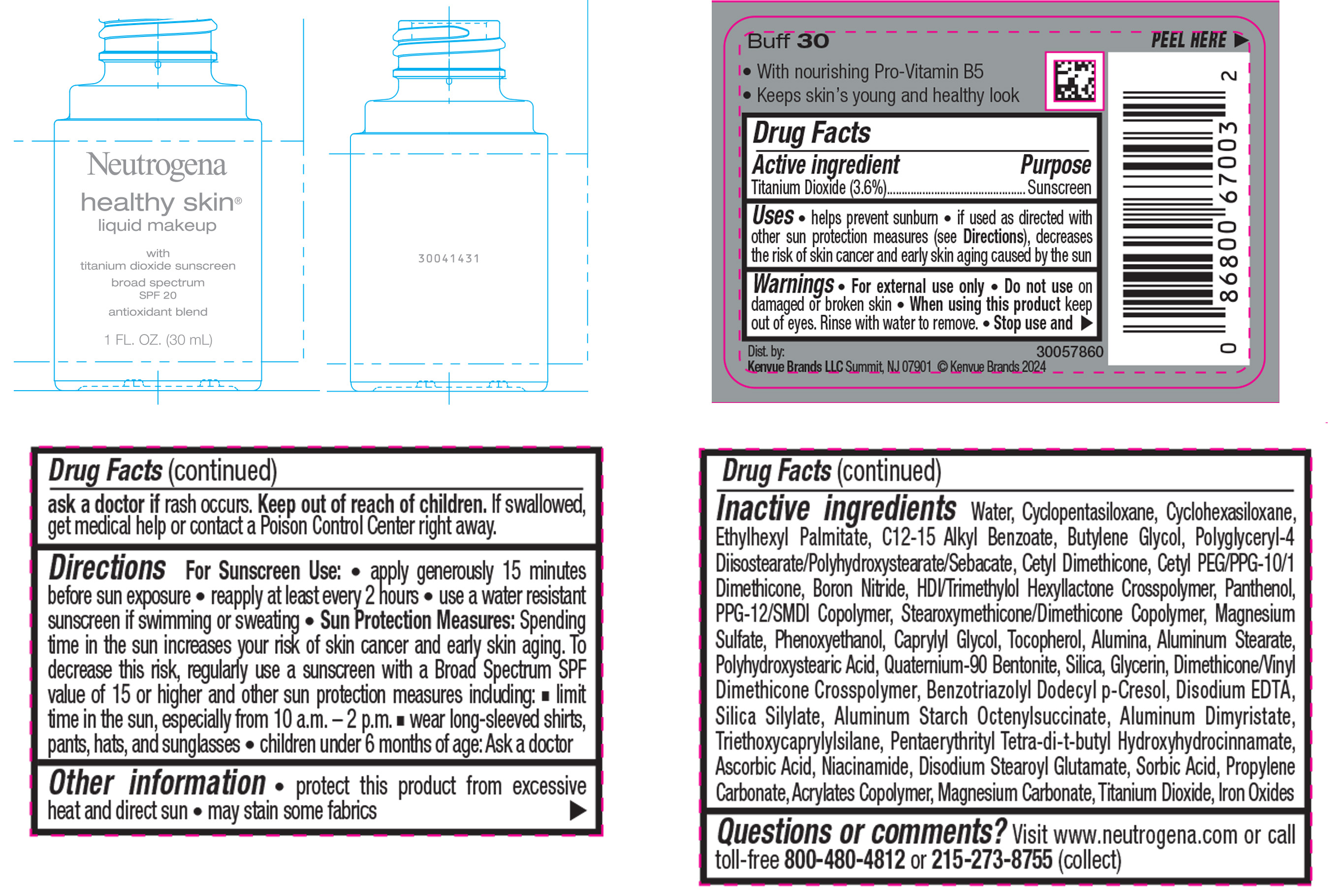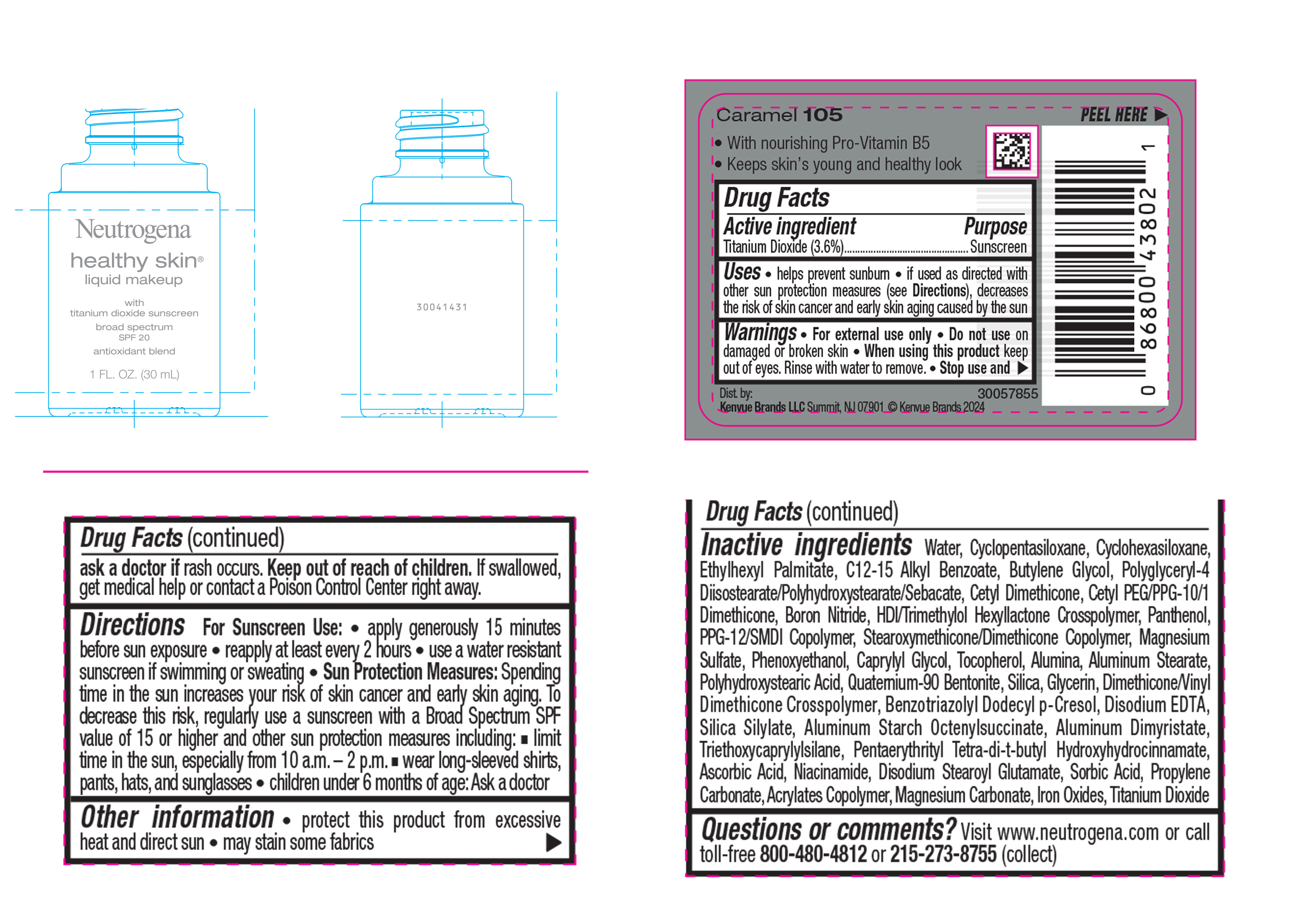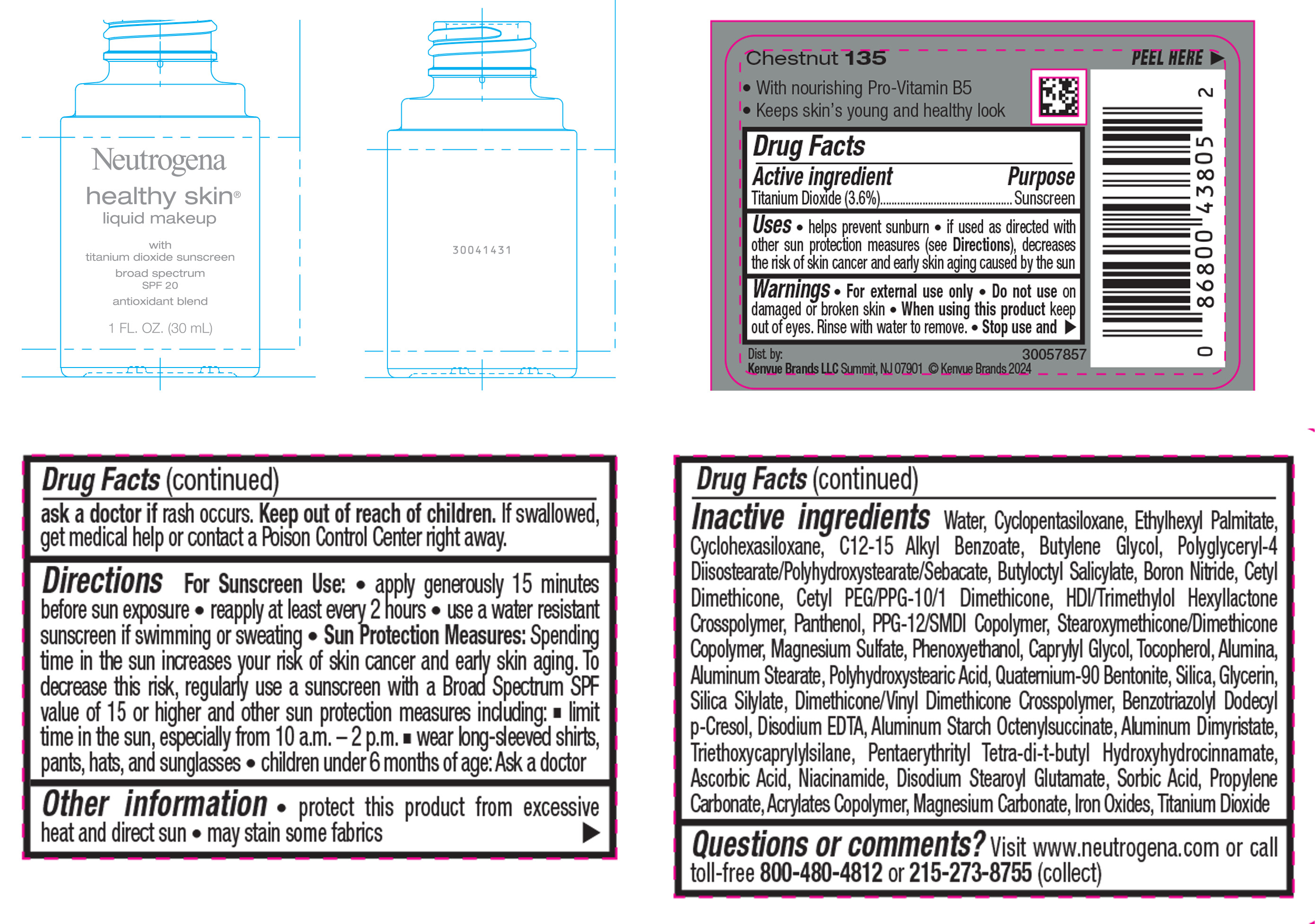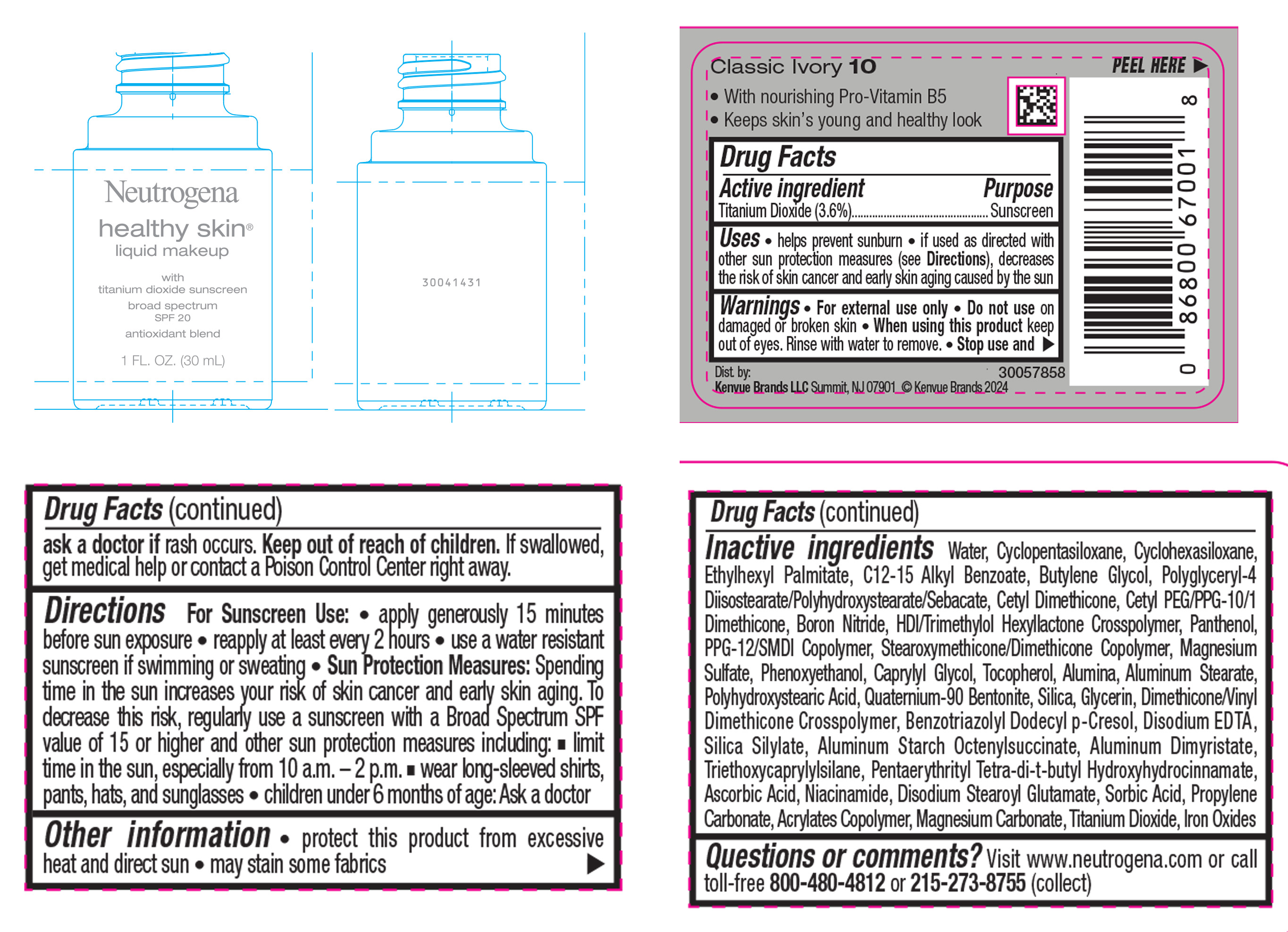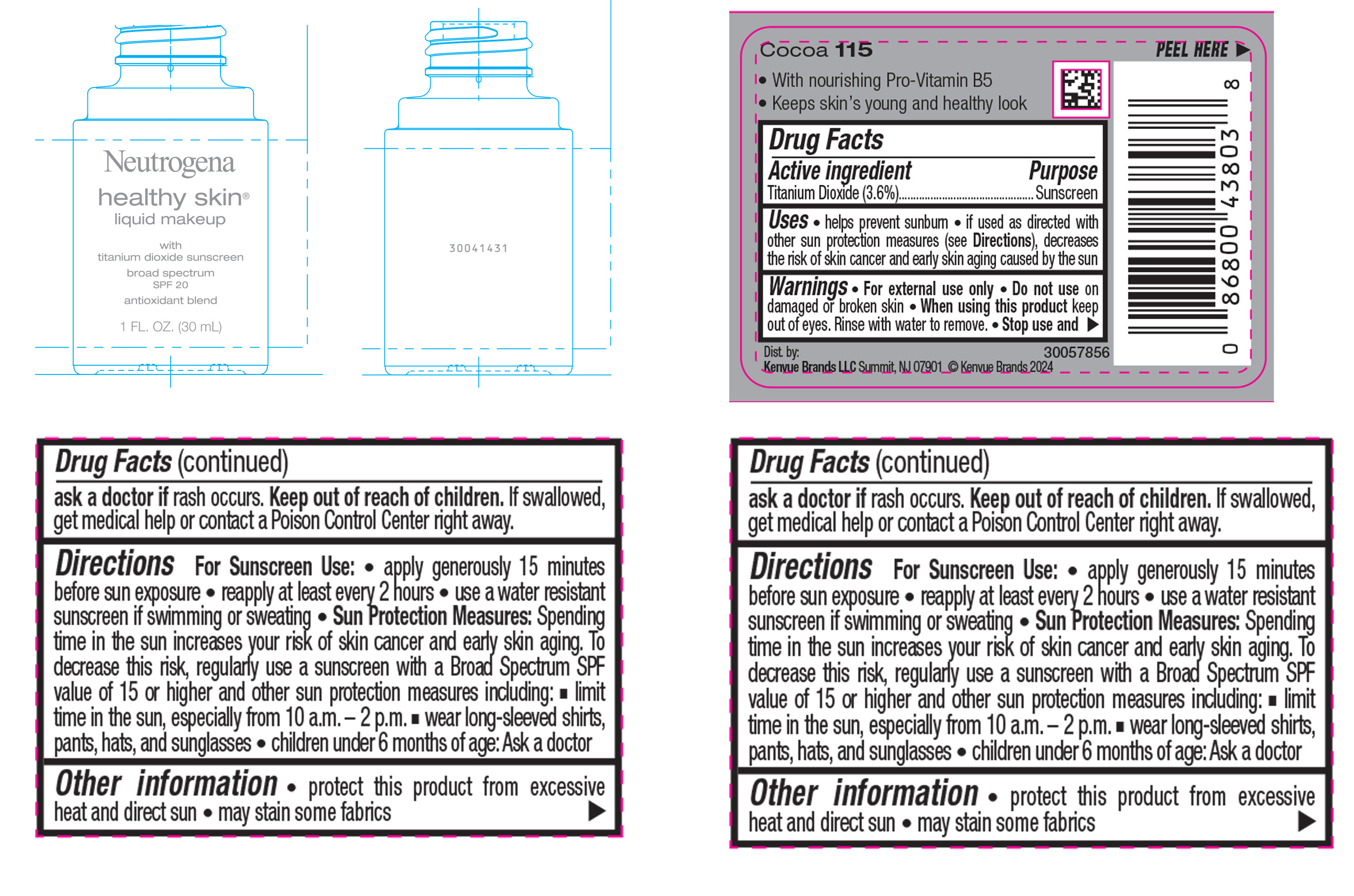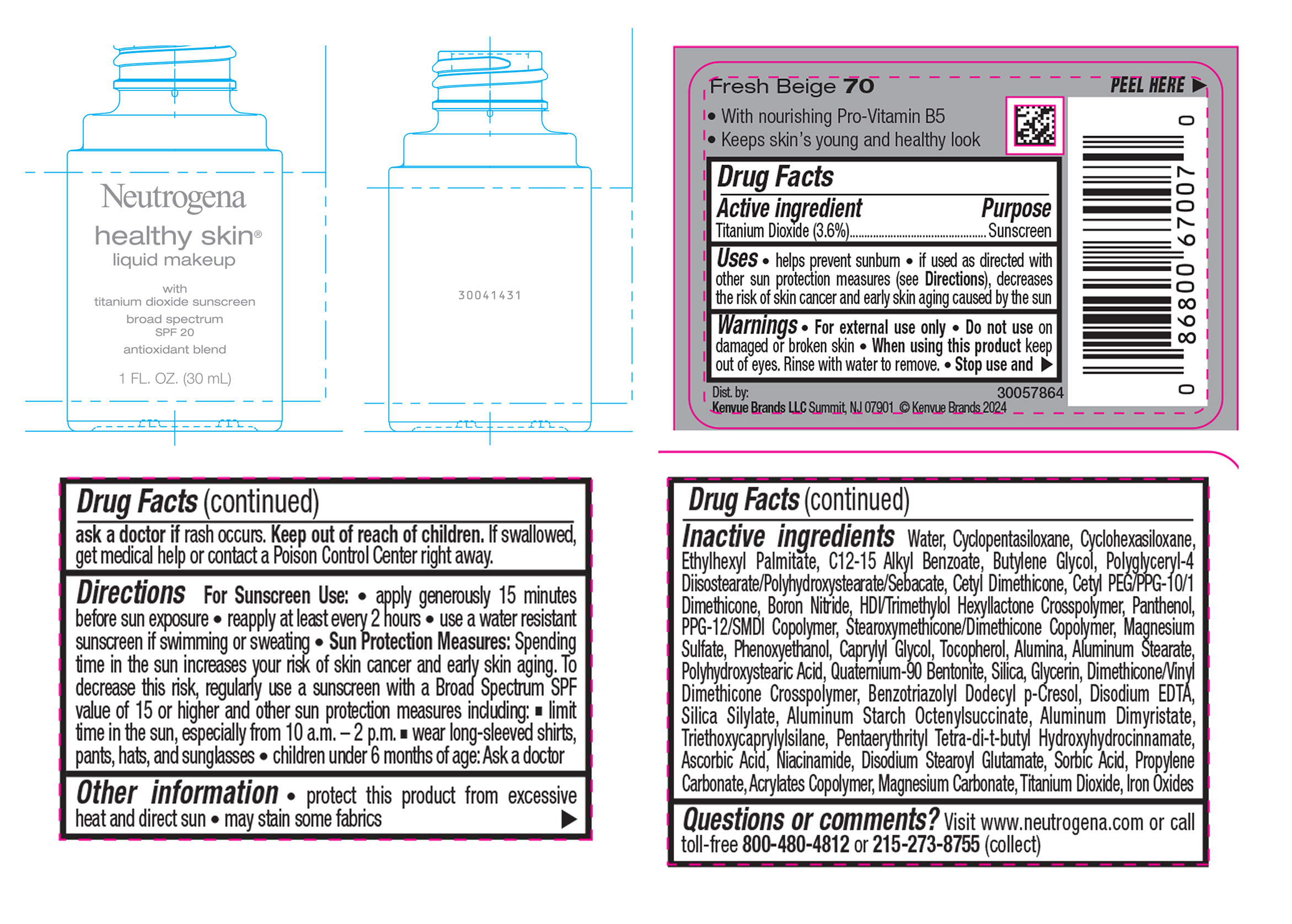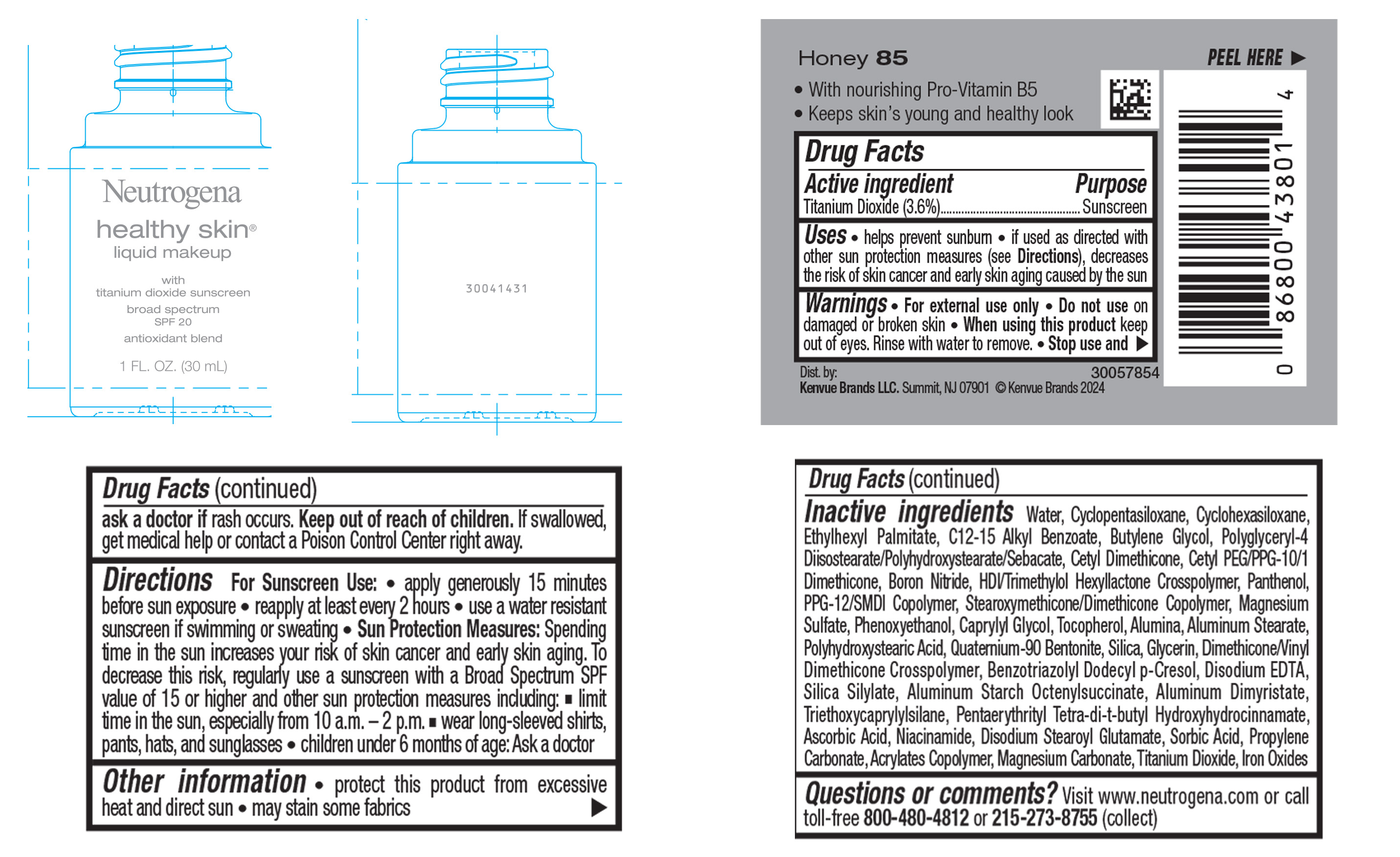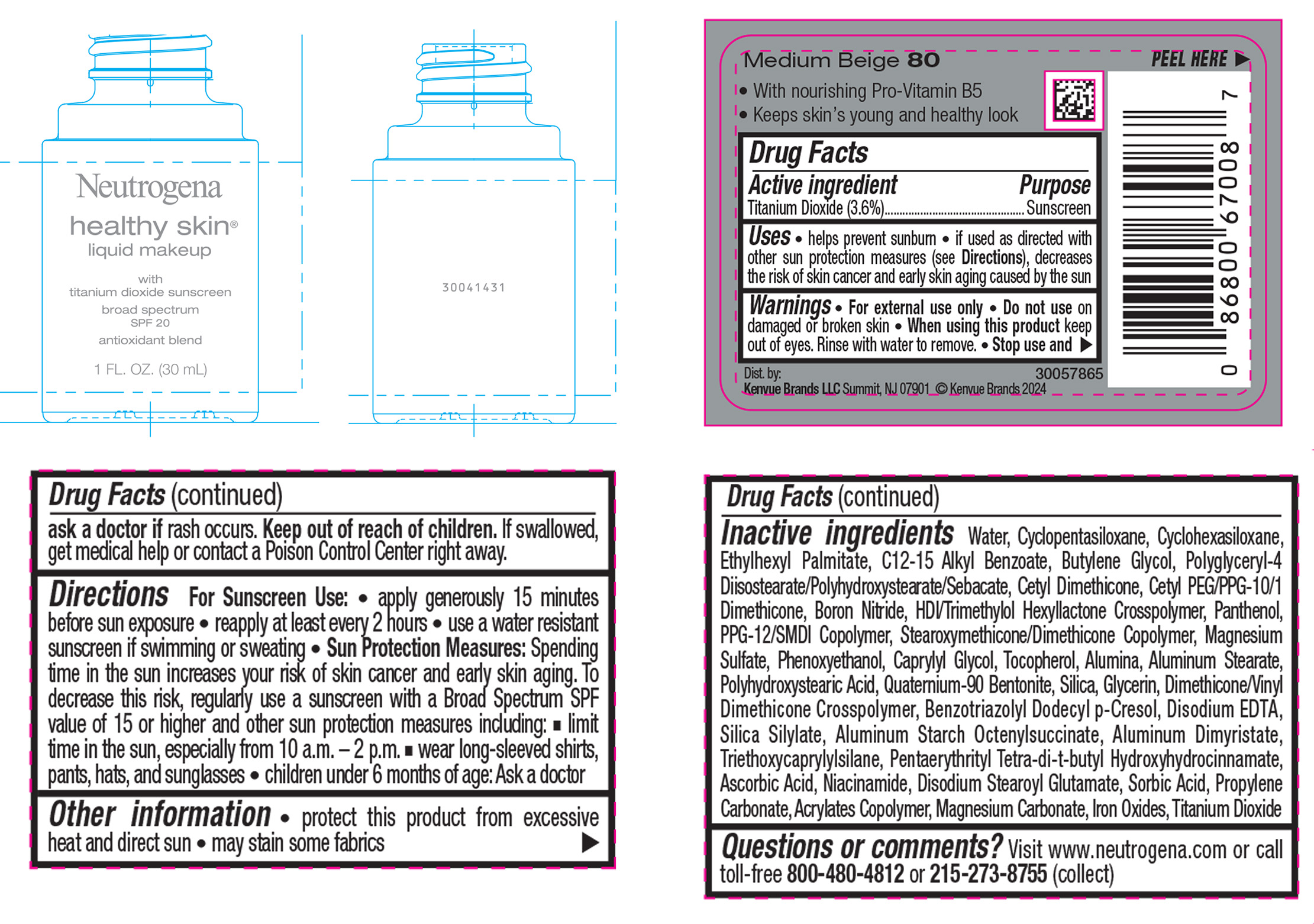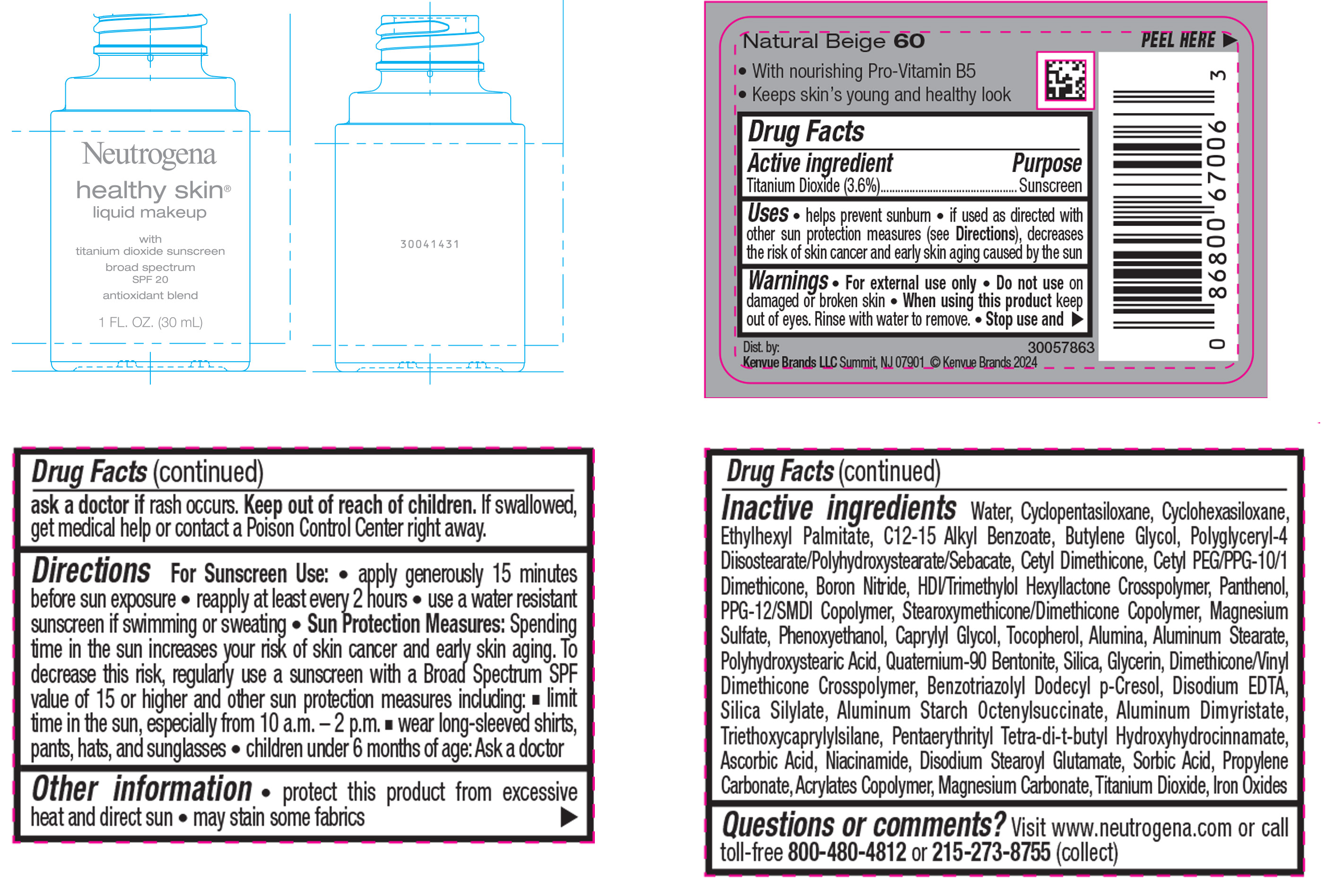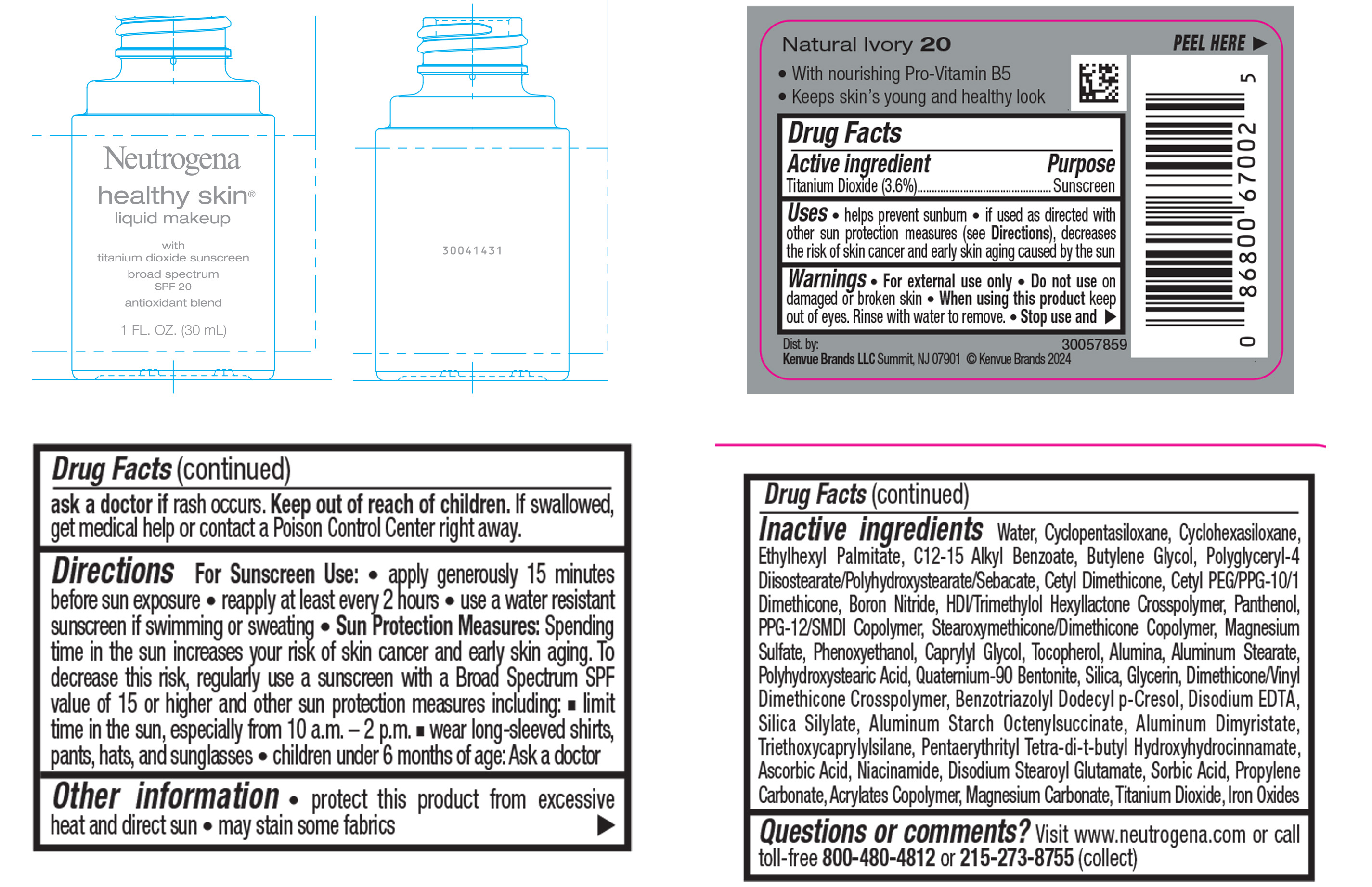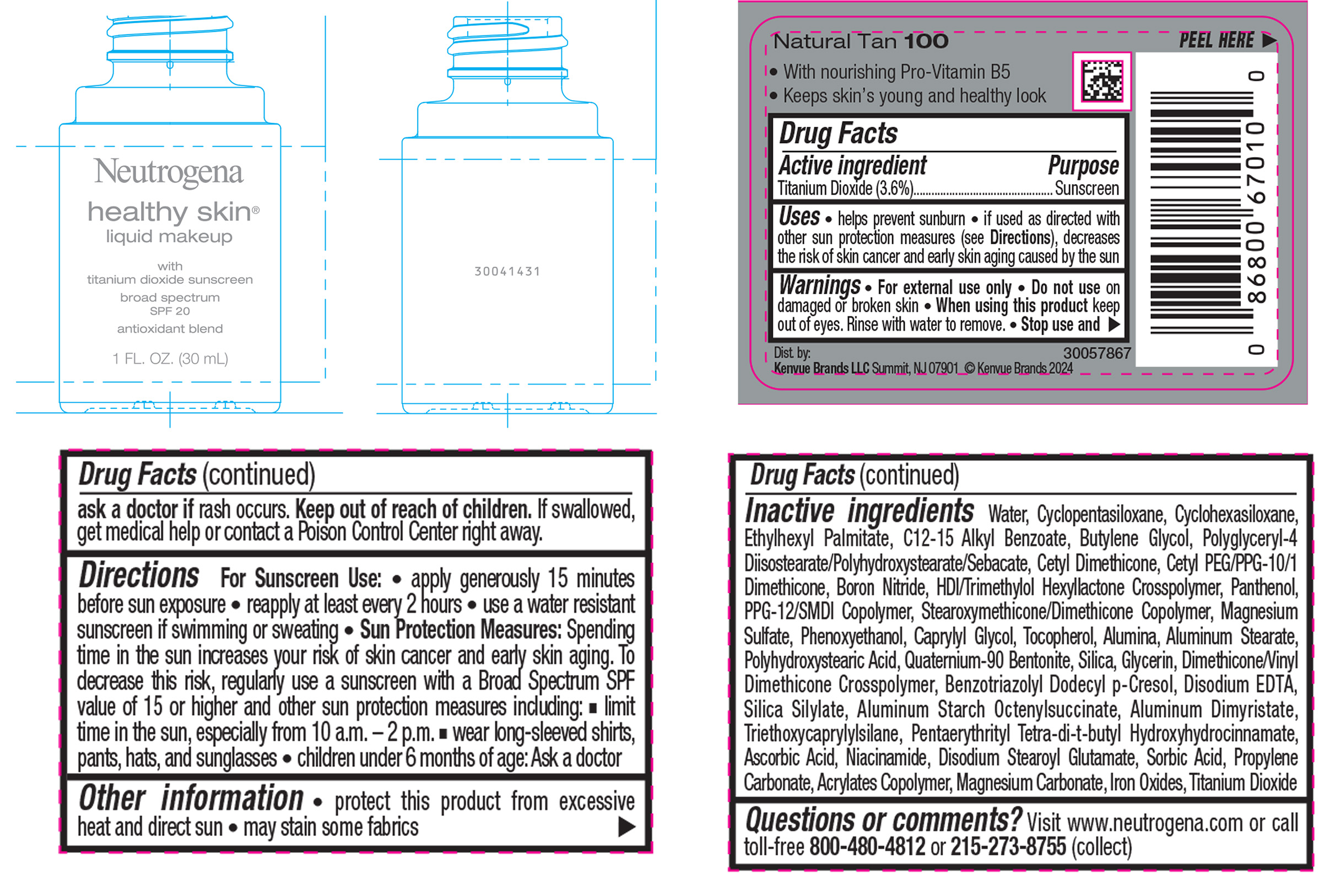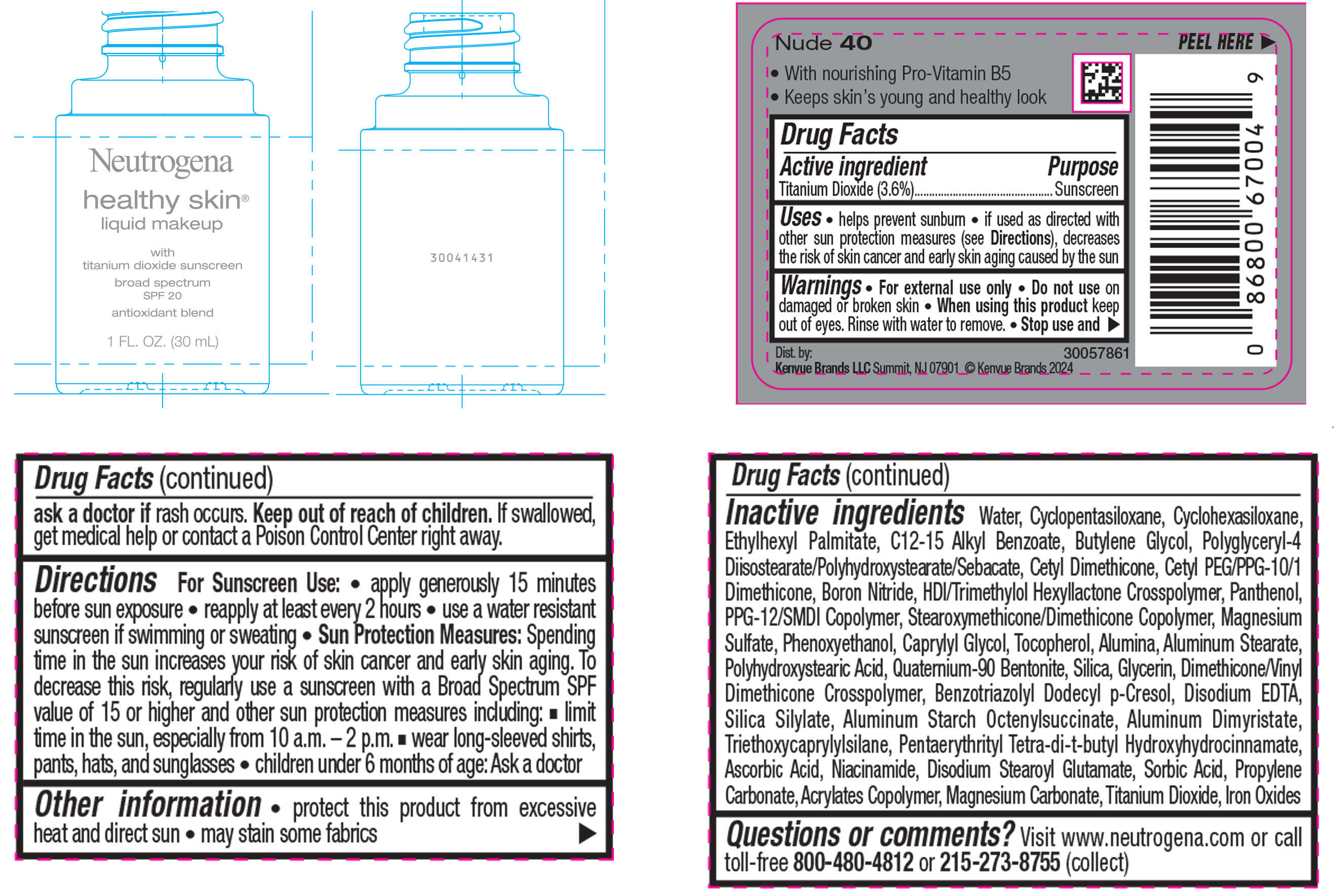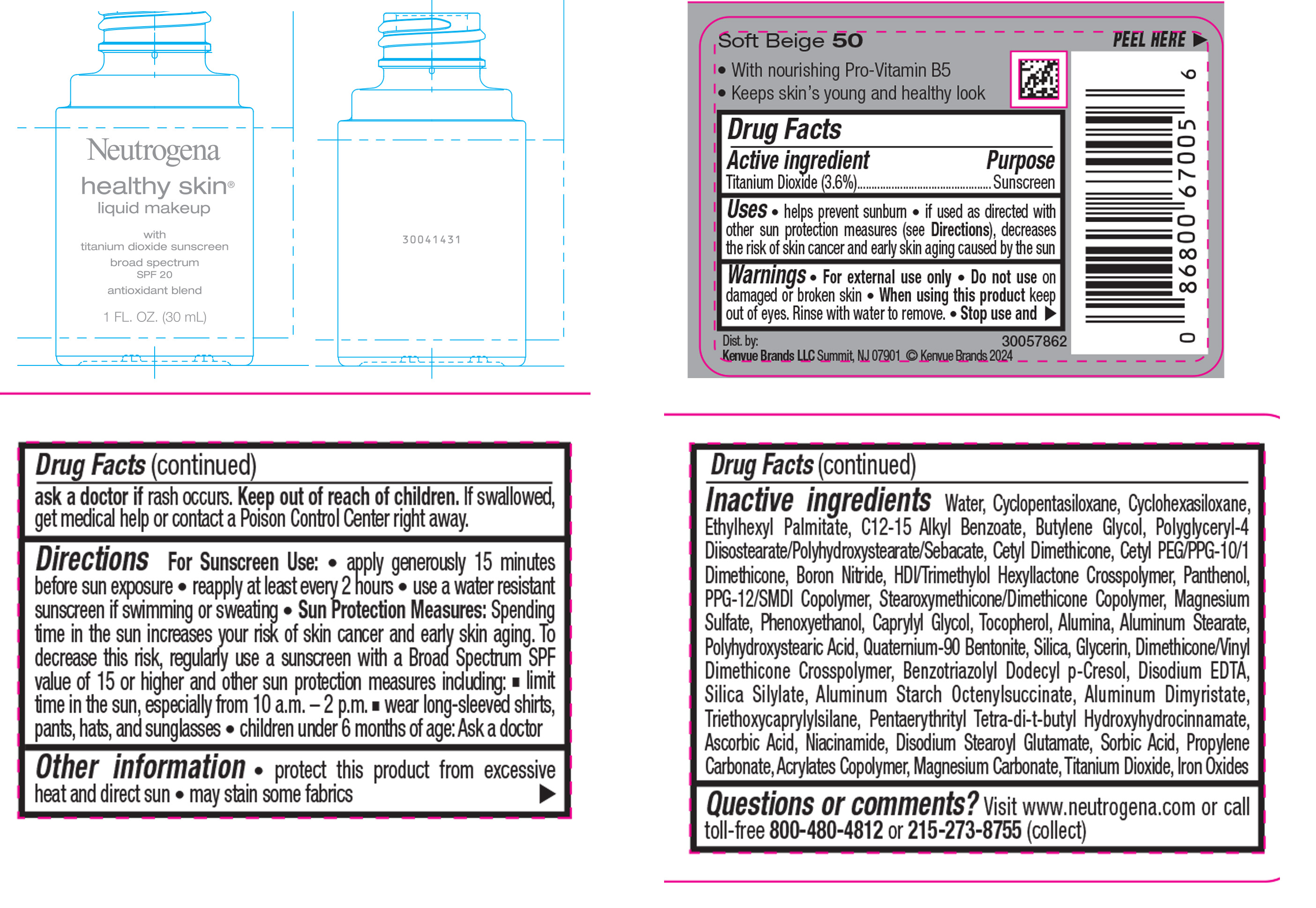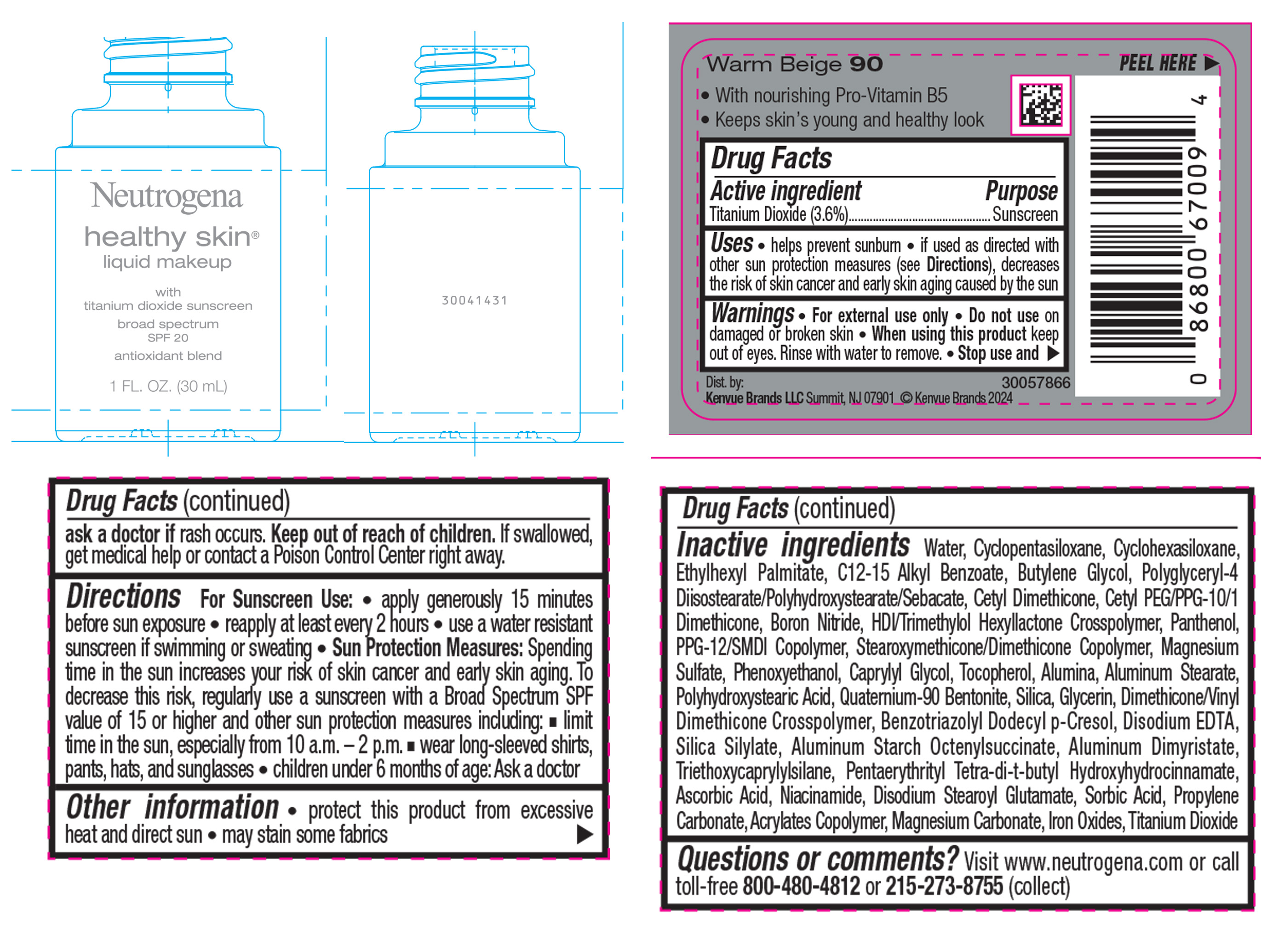 DRUG LABEL: Neutrogena Healthy Skin Liquid Makeup Broad Spectrum SPF 20 - Soft Beige 50
NDC: 69968-0871 | Form: LIQUID
Manufacturer: Kenvue Brands LLC
Category: otc | Type: HUMAN OTC DRUG LABEL
Date: 20241113

ACTIVE INGREDIENTS: TITANIUM DIOXIDE 36 mg/1 mL
INACTIVE INGREDIENTS: CYCLOMETHICONE 5; CYCLOMETHICONE 6; ETHYLHEXYL PALMITATE; BUTYLENE GLYCOL; BORON NITRIDE; HEXAMETHYLENE DIISOCYANATE/TRIMETHYLOL HEXYLLACTONE CROSSPOLYMER; POLYHYDROXYSTEARIC ACID (2300 MW); PENTAERYTHRITOL TETRAKIS(3-(3,5-DI-TERT-BUTYL-4-HYDROXYPHENYL)PROPIONATE); ALKYL (C12-15) BENZOATE; PPG-12/SMDI COPOLYMER; PHENOXYETHANOL; SILICON DIOXIDE; TRIETHOXYCAPRYLYLSILANE; PROPYLENE CARBONATE; BUTYL ACRYLATE/METHYL METHACRYLATE/METHACRYLIC ACID COPOLYMER (18000 MW); FERROUS OXIDE; POLYGLYCERYL-4 DIISOSTEARATE/POLYHYDROXYSTEARATE/SEBACATE; MAGNESIUM SULFATE, UNSPECIFIED; GLYCERIN; ASCORBIC ACID; DISODIUM STEAROYL GLUTAMATE; WATER; TOCOPHEROL; QUATERNIUM-90 BENTONITE; BENZOTRIAZOLYL DODECYL P-CRESOL; ALUMINUM STARCH OCTENYLSUCCINATE; ALUMINUM DIMYRISTATE; MAGNESIUM CARBONATE; ALUMINUM STEARATE; ALUMINUM OXIDE; EDETATE DISODIUM; NIACINAMIDE; SORBIC ACID; PANTHENOL; CAPRYLYL GLYCOL

Neutrogena Healthy Skin Liquid Makeup Broad Spectrum SPF 20

Drug Facts

Active ingredient

Titanium Dioxide 3.6%

Purpose

Sunscreen

Use

• helps prevent sunburn

• if used as directed with other sun protection measures (see Directions), decreases the risk of skin cancer and early skin aging caused by the sun

Warnings

For external use only

- Do not use on damaged or broken skin

- When using this product keep out of eyes. Rinse with water to remove.

Stop use and ask a doctor if rash occurs

Keep out of reach of children. If swallowed, get medical help or contact a Poison Control Center right away.

Directions

For Sunscreen Use:

• apply generously 15 minutes before sun exposure

• reapply at least every 2 hours

• use a water resistant sunscreen if swimming or sweating

• Sun Protection Measures: Spending time in the sun increases your risk of skin cancer and early skin aging. To decrease this risk, regularly use a sunscreen with a Broad Spectrum SPF value of 15 or higher and other sun protection measures including:

▪ limit time in the sun, especially from 10 a.m. – 2 p.m.

▪ wear long-sleeved shirts, pants, hats, and sunglasses

• children under 6 months of age: Ask a doctor

Other information

• protect this product from excessive heat and direct sun

• may stain some fabrics

Inactive ingredients

Water, Cyclopentasiloxane, Cyclohexasiloxane, Ethylhexyl Palmitate, C12-15 Alkyl Benzoate, Butylene Glycol, Polyglyceryl-4 Diisostearate/Polyhydroxystearate/Sebacate, Cetyl Dimethicone, Cetyl PEG/PPG-10/1 Dimethicone, Boron Nitride, HDI/Trimethylol Hexyllactone Crosspolymer, Panthenol, PPG-12/SMDI Copolymer, Stearoxymethicone/Dimethicone Copolymer, Magnesium Sulfate, Phenoxyethanol, Caprylyl Glycol, Tocopherol, Alumina, Aluminum Stearate, Polyhydroxystearic Acid, Quaternium-90 Bentonite, Silica, Glycerin, Dimethicone/Vinyl Dimethicone Crosspolymer, Benzotriazolyl Dodecyl p-Cresol, Disodium EDTA, Silica Silylate, Aluminum Starch Octenylsuccinate, Aluminum Dimyristate, Triethoxycaprylylsilane, Pentaerythrityl Tetra-di-t-butyl Hydroxyhydrocinnamate, Ascorbic Acid, Niacinamide, Disodium Stearoyl Glutamate, Sorbic Acid, Propylene Carbonate, Acrylates Copolymer, Magnesium Carbonate, Titanium Dioxide, Iron Oxides

Questions or Comments?

Visit www.neutrogena.com or call toll-free 800-480-4812 or 215-273-8755 (collect)

Dist. by:

Kenvue Brands LLC. Summit, NJ 07901

Drug Facts

Active ingredient

Titanium Dioxide (3.6%)

Purpose

Sunscreen

Uses

• helps prevent sunburn

• if used as directed with other sun protection measures (see Directions), decreases the risk of skin cancer and early skin aging caused by the sun

Warnings

• For external use only

Do not use on damaged or broken skin

When using this product keep out of eyes. Rinse with water to remove.

Stop use and ask a doctor if rash occurs.

Keep out of reach of children. If swallowed, get medical help or contact a Poison Control Center right away.

Directions

For Sunscreen Use:

• apply generously and evenly 15 minutes before sun exposure

• reapply at least every 2 hours

• use a water resistant sunscreen if swimming or sweating

• Sun Protection Measures: Spending time in the sun increases your risk of skin cancer and early skin aging. To decrease this risk, regularly use a sunscreen with a Broad Spectrum SPF value of 15 or higher and other sun protection measures including:

▪ limit time in the sun, especially from 10 a.m. – 2 p.m.

▪ wear long-sleeved shirts, pants, hats, and sunglasses

• children under 6 months of age: Ask a doctor

Other information

• protect this product from excessive heat and direct sun

• may stain some fabrics

Inactive ingredients

Water, Cyclopentasiloxane, Cyclohexasiloxane, Ethylhexyl Palmitate, C12-15 Alkyl Benzoate, Butylene Glycol, Polyglyceryl-4 Diisostearate/Polyhydroxystearate/Sebacate, Cetyl Dimethicone, Cetyl PEG/PPG-10/1 Dimethicone, Butyloctyl Salicylate, Boron Nitride, HDI/Trimethylol Hexyllactone Crosspolymer, Panthenol, PPG-12/SMDI Copolymer, Stearoxymethicone/ Dimethicone Copolymer, Magnesium Sulfate, Phenoxyethanol, Caprylyl Glycol, Tocopherol, Alumina, Aluminum Stearate, Polyhydroxystearic Acid, Quaternium-90 Bentonite, Silica, Glycerin, Dimethicone/Vinyl Dimethicone Crosspolymer, Benzotriazolyl Dodecyl p-Cresol, Disodium EDTA, Silica Silylate, Aluminum Starch Octenylsuccinate, Aluminum Dimyristate, Triethoxycaprylylsilane, Pentaerythrityl Tetra-di-t-butyl Hydroxyhydrocinnamate, Ascorbic Acid, Niacinamide, Disodium Stearoyl Glutamate, Sorbic Acid, Propylene Carbonate, Acrylates Copolymer, Magnesium Carbonate, Titanium Dioxide, Iron Oxides

Questions or comments?

Visit www.neutrogena.com or call toll free 800-480-4812 or 215-273-8755 (collect)

Dist. by:

Kenvue Brands LLC. Summit, NJ 07901

PRINCIPAL DISPLAY PANEL - 30 mL Bottle Label - Classic Ivory 10

Neutrogena

healthy skin®

liquid makeup

with

titanium dioxide sunscreen

broad spectrum

SPF 20

antioxidant blend

1 FL. OZ. (30 mL)

PRINCIPAL DISPLAY PANEL - 30 mL Bottle Label - Natural Ivory 20

Neutrogena

healthy skin®

liquid makeup

with

titanium dioxide sunscreen

broad spectrum

SPF 20

antioxidant blend

1 FL. OZ. (30 mL)

PRINCIPAL DISPLAY PANEL - 30 mL Bottle Label - Buff 30

Neutrogena

healthy skin®

liquid makeup

with

titanium dioxide sunscreen

broad spectrum

SPF 20

antioxidant blend

1 FL. OZ. (30 mL)

PRINCIPAL DISPLAY PANEL - 30 mL Bottle Label - Nude 40

Neutrogena

healthy skin®

liquid makeup

with

titanium dioxide sunscreen

broad spectrum

SPF 20

antioxidant blend

1 FL. OZ. (30 mL)

PRINCIPAL DISPLAY PANEL - 30 mL Bottle Label - Soft Beige 50

Neutrogena

healthy skin®

liquid makeup

with

titanium dioxide sunscreen

broad spectrum

SPF 20

antioxidant blend

1 FL. OZ. (30 mL)

PRINCIPAL DISPLAY PANEL - 30 mL Bottle Label - Natural Beige 60

Neutrogena

healthy skin®

liquid makeup

with

titanium dioxide sunscreen

broad spectrum

SPF 20

antioxidant blend

1 FL. OZ. (30 mL)

PRINCIPAL DISPLAY PANEL - 30 mL Bottle Label - Fresh Beige 70

Neutrogena

healthy skin®

liquid makeup

with

titanium dioxide sunscreen

broad spectrum

SPF 20

antioxidant blend

1 FL. OZ. (30 mL)

PRINCIPAL DISPLAY PANEL - 30 mL Bottle Label - Medium Beige 80

Neutrogena

healthy skin®

liquid makeup

with

titanium dioxide sunscreen

broad spectrum

SPF 20

antioxidant blend

1 FL. OZ. (30 mL)

PRINCIPAL DISPLAY PANEL - 30 mL Bottle Label - Warm Beige 90

Neutrogena

healthy skin®

liquid makeup

with

titanium dioxide sunscreen

broad spectrum

SPF 20

antioxidant blend

1 FL. OZ. (30 mL)

PRINCIPAL DISPLAY PANEL - 30 mL Bottle Label - Natural Tan 100

Neutrogena

healthy skin®

liquid makeup

with

titanium dioxide sunscreen

broad spectrum

SPF 20

antioxidant blend

1 FL. OZ. (30 mL)

PRINCIPAL DISPLAY PANEL - 30 mL Bottle Label - Honey 85

Neutrogena

healthy skin®

liquid makeup

with

titanium dioxide sunscreen

broad spectrum

SPF 20

antioxidant blend

1 FL. OZ. (30 mL)

PRINCIPAL DISPLAY PANEL - 30 mL Bottle Label - Caramel 105

Neutrogena

healthy skin®

liquid makeup

with

titanium dioxide sunscreen

broad spectrum

SPF 20

antioxidant blend

1 FL. OZ. (30 mL)

PRINCIPAL DISPLAY PANEL - 30 mL Bottle Label - Cocoa 115

Neutrogena

healthy skin®

liquid makeup

with

titanium dioxide sunscreen

broad spectrum

SPF 20

antioxidant blend

1 FL. OZ. (30 mL)

PRINCIPAL DISPLAY PANEL - 30 mL Bottle Label - Chestnut 135

Neutrogena

healthy skin®

liquid makeup

with

titanium dioxide sunscreen

broad spectrum

SPF 20

antioxidant blend

1 FL. OZ. (30 mL)